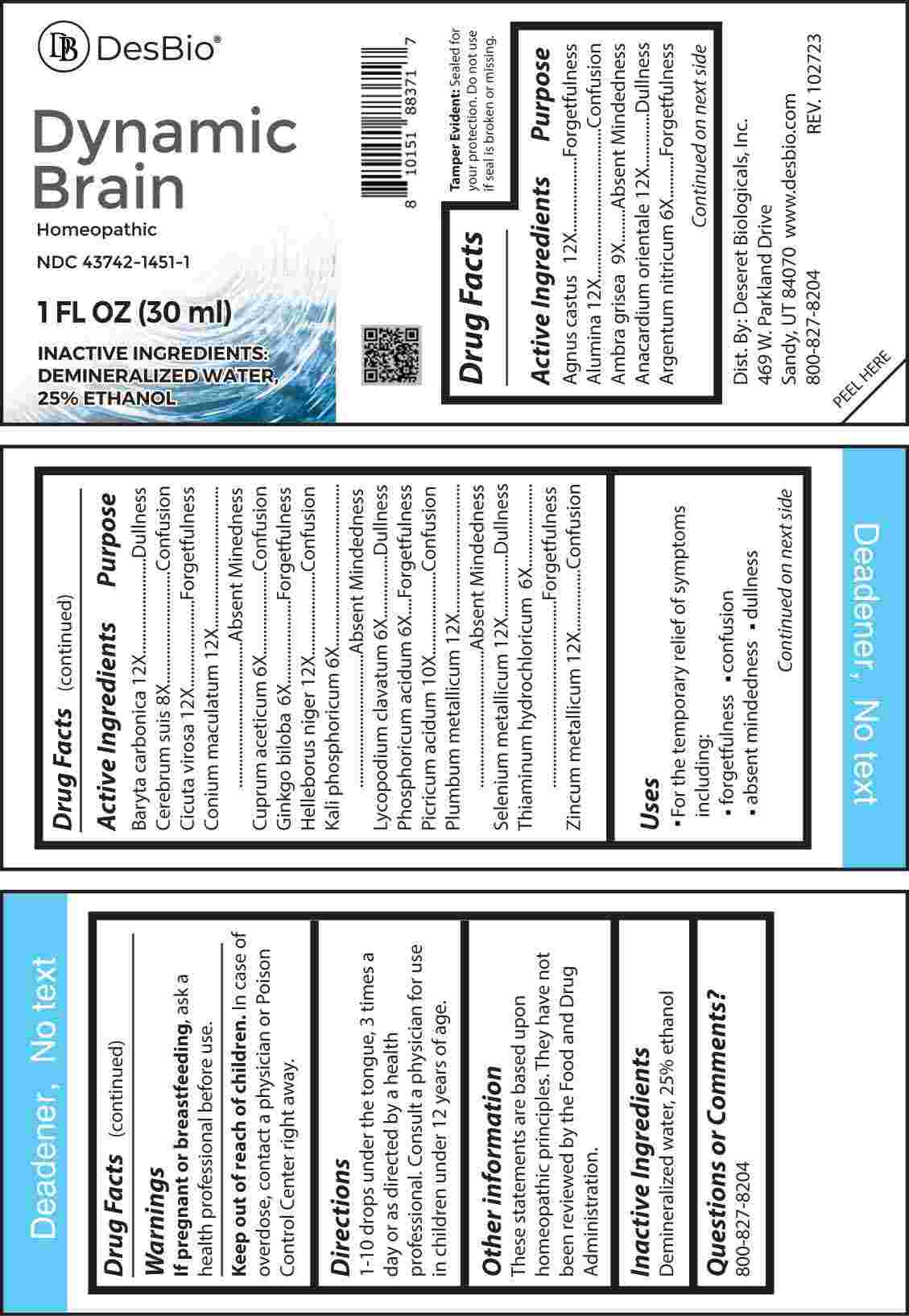 DRUG LABEL: Dynamic Brain
NDC: 43742-1451 | Form: LIQUID
Manufacturer: Deseret Biologicals, Inc.
Category: homeopathic | Type: HUMAN OTC DRUG LABEL
Date: 20240220

ACTIVE INGREDIENTS: SILVER NITRATE 6 [hp_X]/1 mL; CUPRIC ACETATE 6 [hp_X]/1 mL; GINKGO 6 [hp_X]/1 mL; DIBASIC POTASSIUM PHOSPHATE 6 [hp_X]/1 mL; LYCOPODIUM CLAVATUM SPORE 6 [hp_X]/1 mL; PHOSPHORIC ACID 6 [hp_X]/1 mL; THIAMINE HYDROCHLORIDE 6 [hp_X]/1 mL; SUS SCROFA CEREBRUM 8 [hp_X]/1 mL; AMBERGRIS 9 [hp_X]/1 mL; PICRIC ACID 10 [hp_X]/1 mL; CHASTE TREE FRUIT 12 [hp_X]/1 mL; ALUMINUM OXIDE 12 [hp_X]/1 mL; SEMECARPUS ANACARDIUM JUICE 12 [hp_X]/1 mL; BARIUM CARBONATE 12 [hp_X]/1 mL; CICUTA VIROSA ROOT 12 [hp_X]/1 mL; CONIUM MACULATUM FLOWERING TOP 12 [hp_X]/1 mL; HELLEBORUS NIGER ROOT 12 [hp_X]/1 mL; LEAD 12 [hp_X]/1 mL; SELENIUM 12 [hp_X]/1 mL; ZINC 12 [hp_X]/1 mL
INACTIVE INGREDIENTS: WATER; ALCOHOL

DRUG FACTS:

ACTIVE INGREDIENTS:

Agnus Castus 12X, Alumina 12X, Ambra Grisea 9X, Anacardium Orientale 12X, Argentum Nitricum 6X, Baryta Carbonica 12X, Cerebrum Suis 8X, Cicuta Virosa 12X, Conium Maculatum 12X, Cuprum Aceticum 6X, Ginkgo Biloba 6X, Helleborus Niger 12X, Kali Phosphoricum 6X, Lycopodium Clavatum 6X, Phosphoricum Acidum 6X, Picricum Acidum 10X, Plumbum Metallicum 12X, Selenium Metallicum 12X, Thiaminum Hydrochloricum 6X, Zincum Metallicum 12X.

PURPOSE:

Agnus Castus - Forgetfulness, Alumina - Confusion, Ambra Grisea – Absent Mindedness, Anacardium Orientale - Dullness, Argentum Nitricum - Forgetfulness, Baryta Carbonica - Dullness, Cerebrum Suis - Confusion, Cicuta Virosa - Forgetfulness, Conium Maculatum – Absent Mindedness, Cuprum Aceticum - Confusion, Ginkgo Biloba - Forgetfulness, Helleborus Niger -Confusion, Kali Phosphoricum – Absent Mindedness, Lycopodium Clavatum - Dullness, Phosphoricum Acidum - Forgetfulness, Picricum Acidum - Confusion, Plumbum Metallicum – Absent Mindedness, Selenium Metallicum - Dullness, Thiaminum Hydrochloricum - Forgetfulness, Zincum Metallicum - Confusion.

USES:

• For the temporary relief of symptoms including:

• forgetfulness • confusion

• absent-mindedness • dullness

These statements are based upon homeopathic principles. They have not been reviewed by the Food and Drug Administration.

WARNINGS:

If pregnant or breast-feeding, ask a health professional before use.

Keep out of reach of children. In case of overdose, contact a physician or Poison Control Center right away.

Tamper Evident: Sealed for your protection. Do not use if seal is broken or missing.

KEEP OUT OF REACH OF CHILDREN:

In case of overdose, contact physician or a Poison Control Center right away.

DIRECTIONS:

1-10 drops under the tongue, 3 times a day or as directed by a health professional. Consult a physician for use in children under 12 years of age.

INACTIVE INGREDIENTS:

Demineralized water, 25% ethanol

QUESTIONS:

Dist. By: Deseret Biologicals, Inc.
469 W. Parkland Drive
Sandy, UT 84070

www.desbio.com

800-827-8204

PACKAGE LABEL DISPLAY:

DesBio

Dynamic Brain

Homeopathic

NDC 43742-1451-1
1 FL OZ (30 ml)